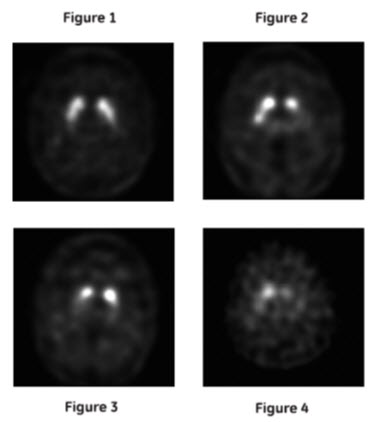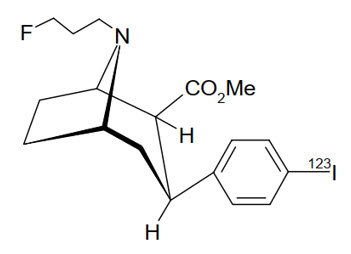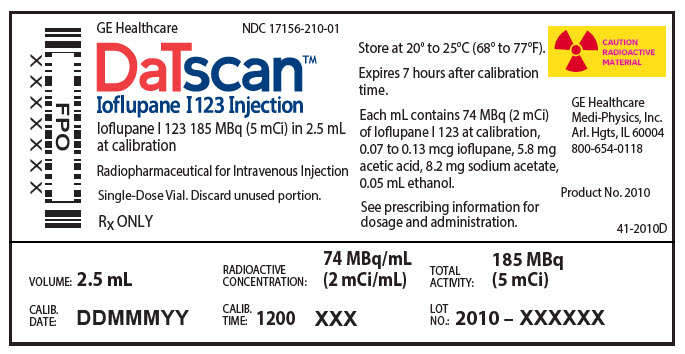 DRUG LABEL: DaTscan
NDC: 17156-210 | Form: INJECTION, SOLUTION
Manufacturer: Medi-Physics Inc. dba GE Healthcare.
Category: prescription | Type: HUMAN PRESCRIPTION DRUG LABEL
Date: 20240110

ACTIVE INGREDIENTS: ioflupane I-123 2 mCi/1 mL
INACTIVE INGREDIENTS: acetic acid 5.8 mg/1 mL; sodium acetate 8.2 mg/1 mL; alcohol 0.05 mg/1 mL

HIGHLIGHTS OF PRESCRIBING INFORMATION

These highlights do not include all the information needed to use DATSCAN safely and effectively. See full prescribing information for DATSCAN.
DATSCAN (ioflupane I 123 injection), for intravenous use
Initial U.S. Approval: 2011

RECENT MAJOR CHANGES

Indications and Usage (1) | 11/2022
Contraindications (4) | 11/2022
Warnings and Precautions, Radiation Risk (5.3) | 11/2022

1 INDICATIONS AND USAGE

DATSCAN is a radioactive diagnostic agent indicated as an adjunct to other diagnostic evaluations for striatal dopamine transporter visualization using single photon emission computed tomography (SPECT) brain imaging in adult patients with:

- suspected Parkinsonian syndromes (PS) or
- suspected dementia with Lewy bodies (DLB). (1)

2 DOSAGE AND ADMINISTRATION

- Administer a thyroid-blocking agent at least one hour before the dose of DATSCAN. (2.2)
- The recommended dose of DATSCAN in adult patients is 111 MBq to 185 MBq (3 mCi to 5 mCi) administered intravenously over at least 20 seconds. (2.3)
- Measure patient dose using a dose calibrator immediately prior to administration. (2.4)
- Begin SPECT imaging between 3 hours and 6 hours post-injection. (2.6)

3 DOSAGE FORMS AND STRENGTHS

Injection: 185 MBq (5 mCi) in 2.5 mL at a concentration of 74 MBq/mL (2 mCi/mL) of ioflupane I 123 at calibration date and time supplied in single-dose vials. (3)

4 CONTRAINDICATIONS

Known serious hypersensitivity to ioflupane I 123 (4)

5 WARNINGS AND PRECAUTIONS

- Hypersensitivity Reactions: Hypersensitivity reactions including dyspnea, edema, rash, erythema, and pruritus have been reported. Have treatment measures available prior to DATSCAN administration. (5.1)
- Thyroid Accumulation of Iodine-123: Thyroid uptake of iodine-123 may result in an increased long-term risk for thyroid neoplasia. (2.2, 5.2)
- Radiation Risk: Ensure safe handling to minimize radiation exposure to the patient and healthcare providers. Advise patients to hydrate before and after administration and to void frequently after administration. (2.1, 5.3)

6 ADVERSE REACTIONS

The following adverse reactions were reported at ≤1%: headache, nausea, vertigo, dry mouth and dizziness. (6.1)

To report SUSPECTED ADVERSE REACTIONS, contact GE Healthcare at 1-800-654-0118 or FDA at 1-800-FDA-1088 or www.fda.gov/medwatch.

7 DRUG INTERACTIONS

Amoxapine, amphetamine, armodafinil, benztropine, bupropion, buspirone, cocaine, mazindol, methamphetamine, methylphenidate, modafinil norephedrine, phentermine, phenylpropanolamine, selegiline, sertraline, citalopram and paroxetine may interfere with DATSCAN imaging. The effects of dopamine agonists and antagonists on DATSCAN imaging have not been established. (7)

8 USE IN SPECIFIC POPULATIONS

- Pregnancy: May cause fetal harm. (8.1)
- Lactation: Advise a lactating woman to interrupt breastfeeding and pump and discard breastmilk for at least 6 days after DATSCAN administration. (8.2)

FULL PRESCRIBING INFORMATION

1 INDICATIONS AND USAGE

DATSCAN is indicated as an adjunct to other diagnostic evaluations for striatal dopamine transporter visualization using single photon emission computed tomography (SPECT) brain imaging in adult patients with:

- suspected Parkinsonian syndromes (PS) or
- suspected dementia with Lewy bodies (DLB).

2 DOSAGE AND ADMINISTRATION

2.1 Radiation Safety

DATSCAN emits radiation and must be handled with safety measures to minimize radiation exposure to healthcare providers and patients [see Warnings and Precautions (5.3)]. Radiopharmaceuticals should be used by or under the control of healthcare providers who are qualified by specific training and experienced in the safe use and handling of radionuclides, and whose experience and training have been approved by the appropriate government agency authorized to license the use of radionuclides.

To minimize radiation exposure, encourage hydration prior to and following DATSCAN administration in order to permit frequent voiding. Encourage the patient to void frequently for the first 48 hours following DATSCAN administration [see Dosage and Administration (2.5)].

2.2 Thyroid Blockade Before DATSCAN Administration

Administer Potassium Iodide Oral Solution or Strong Iodine Solution (e.g., Lugol's Solution) equivalent to 100 mg iodide to block uptake of iodine-123 by the patient's thyroid at least one hour before the dose of DATSCAN [see Warnings and Precautions (5.2)].

2.3 Recommended Dosage

The recommended dose of DATSCAN in adult patients is 111 MBq to 185 MBq (3 mCi to 5 mCi) administered intravenously over at least 20 seconds.

2.4 Preparation and Administration

- Assess pregnancy status before administering DATSCAN to a female of reproductive potential [see Use in Specific Populations (8.1)].
- Use aseptic procedures and radiation shielding during preparation and administration.
- Inspect the DATSCAN vial for particulate matter and discoloration prior to administration and do not use it if the vial contains particulate matter or discoloration.
- Measure patient dose using a dose calibrator immediately prior to administration.
- Discard unused portion.

2.5 Radiation Dosimetry

The estimated radiation absorbed doses to an adult from intravenous injection of DATSCAN are shown in Table 1. The values are calculated assuming urinary bladder emptying at 4.8-hour intervals and appropriate thyroid blocking (iodine-123 is a known Auger electron emitter).

Table 1 Estimated Radiation Absorbed Doses from DATSCAN
 | ORGAN / TISSUE | ABSORBED DOSE PER UNIT ADMINISTERED ACTIVITY (µGy / MBq)
 | Adrenals | 12.9
 | Brain | 17.8
 | Striata | 230
 | Breasts | 7.8
 | Gallbladder Wall | 26.4
GI Tract | Esophagus | 10
GI Tract | Stomach Wall | 11.2
GI Tract | Small Intestine Wall | 21.2
GI Tract | Colon Wall [The absorbed dose to the colon wall is the mass-weighted sum of the absorbed doses to the upper and lower large intestine walls, Dcolon = 0.57DULI + 0.43DLLI [Publication 80 of the ICRP (International Commission on Radiological Protection); Annals of the ICRP 28 (3). Oxford: Pergamon Press; 1998]] | 39.8
GI Tract | Upper Large Intestine Wall | 38.1
GI Tract | Lower Large Intestine Wall | 42
 | Heart Wall | 12.9
 | Kidneys | 10.9
 | Liver | 27.9
 | Lungs | 41.2
 | Muscle | 9.4
 | Osteogenic Cells | 28.2
 | Ovaries | 16.8
 | Pancreas | 13
 | Red Marrow | 9.2
 | Skin | 6
 | Spleen | 10.4
 | Testes | 8.5
 | Thymus | 10
 | Thyroid | 9
 | Urinary Bladder Wall | 53.1
 | Uterus | 16.1
 | Total Body | 11.3
EFFECTIVE DOSE PER UNIT ADMINISTERED ACTIVITY (µSv/MBq) |  | 21.3

The Effective Dose resulting from a DATSCAN administration with an administered activity of 185 MBq (5 mCi) is 3.94 mSv in an adult.

2.6 Imaging Instructions

Begin SPECT imaging 3 hours to 6 hours following DATSCAN administration.

Use a gamma camera fitted with high-resolution collimators and set to a photopeak of 159 keV with a ± 10% energy window. Angular sampling should be at least 120 views over 360 degrees.

Position the patient supine with the head on an off-the-table headrest, use a flexible head restraint such as a strip of tape across the chin or forehead if necessary to help avoid movement, and set a circular orbit for the detector heads with the radius as small as possible (typically 11 cm to 15 cm).

Obtain images with matrix size and zoom factors selected to give a pixel size of 3.5 mm to 4.5 mm. Collect a minimum of 1.5 million counts for optimal images.

2.7 Image Interpretation

Interpret DATSCAN images visually, based upon the appearance of the striata. Reconstructed pixel size should be between 3.5 mm and 4.5 mm with slices 1 pixel thick. Optimum presentation of the reconstructed images for visual interpretation is transaxial slices parallel to the anterior commissure-posterior commissure (AC-PC) line.

Determine whether an image is normal or abnormal by assessing the extent (as indicated by shape) and intensity of the striatal signal. Image interpretation does not involve integration of the striatal image appearance with clinical signs and/or symptoms.

Normal: In transaxial images, normal images are characterized by two symmetric comma- or crescent-shaped focal regions of activity mirrored about the median plane. Striatal activity is distinct, relative to surrounding brain tissue (Figure 1).

Abnormal: Abnormal DATSCAN images fall into at least one of the following three categories (all are considered abnormal).

- Activity is asymmetric, e.g., activity in the region of the putamen of one hemisphere is absent or greatly reduced with respect to the other. Activity is still visible in the caudate nuclei of both hemispheres resulting in a comma or crescent shape in one and a circular or oval focus in the other. There may be reduced activity between at least one striatum and surrounding tissues (Figure 2).
- Activity is absent in the putamen of both hemispheres and confined to the caudate nuclei. Activity is relatively symmetric and forms two roughly circular or oval foci. Activity of one or both is generally reduced (Figure 3).
- Activity is absent in the putamen of both hemispheres and greatly reduced in one or both caudate nuclei. Activity of the striata with respect to the background is reduced (Figure 4).

3 DOSAGE FORMS AND STRENGTHS

Injection: clear, colorless solution containing 185 MBq (5 mCi) in 2.5 mL at a concentration of 74 MBq/mL (2 mCi/mL) of ioflupane I 123 at calibration date and time supplied in single-dose vials.

4 CONTRAINDICATIONS

DATSCAN is contraindicated in patients with known serious hypersensitivity to ioflupane I 123 [see Warnings and Precautions (5.1)].

5 WARNINGS AND PRECAUTIONS

5.1 Hypersensitivity Reactions

Hypersensitivity reactions, including dyspnea, edema, rash, erythema, and pruritus, have been reported following DATSCAN administration [see Adverse Reactions (6.2)]. The reactions have generally occurred within minutes of DATSCAN administration and have either resolved spontaneously or following the administration of corticosteroids and antihistamines.

DATSCAN is contraindicated in patients with known serious hypersensitivity to ioflupane I 123 [see Contraindications (4)]. Have treatment measures available and monitor patients for symptoms or signs of a hypersensitivity reaction.

5.2 Thyroid Accumulation of Iodine-123

DATSCAN may contain up to 6% of free iodide (iodine-123). Thyroid uptake of iodine-123 may result in an increased long-term risk for thyroid neoplasia. To decrease thyroid accumulation of iodine-123, block the thyroid gland before administration of DATSCAN [see Dosage and Administration (2.2)].

5.3 Radiation Risk

DATSCAN contributes to a patient's overall long-term cumulative radiation exposure. Long-term cumulative radiation exposure is associated with an increased risk for cancer. Ensure safe handling to minimize radiation exposure to patients and healthcare providers. Advise patients to hydrate before and after administration and to void frequently after administration [see Dosage and Administration (2.1)].

6 ADVERSE REACTIONS

The following clinically significant adverse reaction is described elsewhere in the labeling:

- Hypersensitivity Reactions [see Warnings and Precautions (5.1)]

6.1 Clinical Trials Experience

Because clinical trials are conducted under widely varying conditions, adverse reaction rates observed in the clinical trials of DATSCAN cannot be directly compared to rates in the clinical trials of another drug and may not reflect the rates observed in practice.

The data from clinical trials reflect exposure to DATSCAN in 942 subjects with a mean age of 66 years (range 25 years to 90 years). Among these subjects, 42% were female and 99% White. Subjects received 88 MBq to 287 MBq (2 mCi to 8 mCi) [median 173 MBq (4.7 mCi)] intravenously as a single dose. The recommended dose of DATSCAN is 111 MBq to 185 MBq (3 mCi to 5 mCi) [see Dosage and Administration (2.3)].

The following adverse reactions were reported at a rate of 1% or less: headache, nausea, vertigo, dry mouth, and dizziness.

6.2 Postmarketing Experience

The following adverse reactions have been identified during postapproval use of DATSCAN. Because these reactions are reported voluntarily from a population of uncertain size, it is not always possible to reliably estimate their frequency or establish a causal relationship to drug exposure.

Immune system disorders: Hypersensitivity, including dyspnea, edema, rash, erythema, and pruritus

General disorders and administration site conditions: Injection site pain

7 DRUG INTERACTIONS

Ioflupane I 123 binds to the dopamine transporter [see Clinical Pharmacology (12.1)]. Drugs that bind to the dopamine transporter with high affinity may interfere with the image obtained following DATSCAN administration. These potentially interfering drugs consist of: amoxapine, amphetamine, armodafinil, benztropine, bupropion, buspirone, cocaine, mazindol, methamphetamine, methylphenidate, modafinil, norephedrine, phentermine, phenylpropanolamine, selegiline, and sertraline. Selective serotonin reuptake inhibitors (paroxetine and citalopram) may increase or decrease ioflupane binding to the dopamine transporter. Whether discontinuation of these drugs prior to DATSCAN administration may minimize the interference with a DATSCAN image is unknown.

The impact of dopamine agonists and antagonists upon DATSCAN imaging results has not been established.

8 USE IN SPECIFIC POPULATIONS

8.1 Pregnancy

Risk Summary

Radioactive iodine products cross the placenta and can permanently impair fetal thyroid function. Administration of an appropriate thyroid blocking agent is recommended before use of DATSCAN in a pregnant woman to protect the woman and fetus from accumulation of iodine-123 [see Dosage and Administration (2.2)].

There are no available data on DATSCAN use in pregnant women to evaluate for a drug-associated risk of major birth defects, miscarriage or adverse maternal or fetal outcomes. Animal reproduction studies have not been conducted with ioflupane I 123. All radiopharmaceuticals have the potential to cause fetal harm depending on the fetal stage of development and the magnitude of the radiation dose. Administration of DATSCAN at a dose of 185 MBq (5 mCi) results in an absorbed radiation dose to the uterus of 0.3 rad (3.0 mGy). Radiation doses greater than 15 rad (150 mGy) have been associated with congenital anomalies but doses under 5 rad (50 mGy) generally have not. Advise pregnant women of the potential risks of fetal exposure to radiation doses with administration of DATSCAN.

The estimated background risk of major birth defects and miscarriage for the indicated population(s) is unknown. All pregnancies have a background risk of birth defect, loss, or other adverse outcomes. In the U.S. general population, the estimated background risk of major birth defects and miscarriage in clinically recognized pregnancies is 2% to 4% and 15% to 20%, respectively.

8.2 Lactation

Risk Summary

Iodine-123, the radionuclide in DATSCAN, is present in human milk. There is no information on the effects on the breastfed infant or on milk production. Advise a lactating woman to interrupt breastfeeding and pump and discard breastmilk for at least 6 days (>10 physical half-lives) after DATSCAN administration in order to minimize radiation exposure to a breastfed infant.

8.4 Pediatric Use

The safety and efficacy of DATSCAN have not been established in pediatric patients.

8.5 Geriatric Use

In the two principal clinical studies of DATSCAN for suspected Parkinsonian syndromes, 45% of the subjects were aged 65 and over, while 10% were 75 and over [see Clinical Studies (14.1)]. No overall differences in safety or effectiveness were observed between these subjects and younger subjects. Other reported clinical experience has not identified differences in responses between the elderly and younger patients.

8.6 Renal Impairment

DATSCAN is excreted by the kidney and patients with severe renal impairment may have increased radiation exposure and altered DATSCAN images.

10 OVERDOSAGE

The risks of overdose relate predominantly to increased radiation exposure, with the long-term risks for neoplasia. In case of overdosage of radioactivity, frequent urination and defecation should be encouraged to minimize radiation exposure to the patient.

11 DESCRIPTION

11.1 Chemical Characteristics

DATSCAN (ioflupane I 123 injection) is a sterile, pyrogen-free radioactive diagnostic agent for intravenous use. DATSCAN is a clear and colorless solution supplied in single-dose vials. Each milliliter contains 0.07 to 0.13 mcg ioflupane, 74 MBq (2 mCi) of iodine-123 (as ioflupane I 123) at calibration time, 5.8 mg acetic acid, 8.2 mg sodium acetate and 0.05 mL (5%) ethanol. The pH of the solution is between 4.2 and 5.2.

The chemical name for ioflupane I 123 is N-ω-fluoropropyl-2β-carbomethoxy-3β-(4-[^123I]iodophenyl)nortropane and it has the following structural formula:

11.2 Physical Characteristics

Iodine-123 is a cyclotron-produced radionuclide that decays to tellurium-123 by electron capture and has a physical half-life of 13.2 hours. The photon that is useful for detection and imaging studies is listed in Table 2.

Table 2 Principal Radiation Emission Data – Iodine-123
Radiation | Energy Level (keV) | Abundance (%)
Gamma | 159 | 83

11.3 External Radiation

The specific gamma-ray constant for iodine-123 is 1.6 R/mCi-hr at 1 cm. The first half-value thickness of lead (Pb) for iodine-123 is 0.04 cm. The relative transmission of radiation emitted by the radionuclide that results from interposition of various thicknesses of Pb is shown in Table 3 (e.g., the use of 2.16 cm Pb will decrease the external radiation exposure by a factor of about 1,000).

Table 3 Reduction in In-air Collision Kerma Caused by Lead Shielding [Calculation based on attenuation and energy-transfer coefficients obtained from National Institute of Standards & Technology Internal Report NISTIR 5632.]
Shield Thickness cm of lead (Pb) | Reduction in In-air Collision Kerma
0.04 | 0.5
0.13 | 10^-1
0.77 | 10^-2
2.16 | 10^-3
3.67 | 10^-4

12 CLINICAL PHARMACOLOGY

12.1 Mechanism of Action

The active drug substance in DATSCAN is N-ω-fluoropropyl-2β-carbomethoxy-3β-(4-[^123I]iodophenyl)nortropane or ioflupane I 123.

In vitro, ioflupane binds reversibly to the human dopamine transporter (DaT) (Ki = 0.62 nM; IC50 = 0.71 nM). Autoradiography of post-mortem human brain slices exposed to radiolabeled ioflupane shows concentration of the radiolabel in striatum (caudate nucleus and putamen). The specificity of the binding of ioflupane I 125 to dopamine transporter was demonstrated by competition studies with the DaT inhibitor GBR 12909 (a dopamine reuptake inhibitor), the serotonin reuptake inhibitor citalopram, and the norepinephrine reuptake inhibitor desipramine in post-mortem human brain slices exposed to radiolabeled ioflupane. Citalopram reduced binding in the neocortex and thalamus with only minor effects in the striatum. This indicated that the binding in the cortex and thalamus is mainly to the serotonin reuptake sites. Desipramine showed no effect on the level of striatal binding of ioflupane I 125, but reduced extrastriatal binding by 60 to 85%. The binding of ioflupane I 125 to the striatum was abolished in the presence of high concentrations of GBR 12909, indicating selectivity of ioflupane binding for the pre-synaptic DaT.

Following administration of DATSCAN to humans, radioactive decay of the iodine-123 emits gamma radiation which can be detected externally using gamma detectors, allowing visualization of the brain striata through SPECT imaging [see Clinical Pharmacology (12.3)].

12.2 Pharmacodynamics

As DATSCAN contains a very small quantity of ioflupane, no ioflupane pharmacologic effects are expected [see Description (11)].

12.3 Pharmacokinetics

The pharmacokinetics of ioflupane I 123 were studied by monitoring radioactivity following intravenous injection; only 5% of the administered radioactivity remained in whole blood at 5 minutes post-injection. Uptake in the brain reached approximately 7% of injected radioactivity at 10 minutes post-injection and decreased to 3% after 5 hours; striata to background ratios were relatively constant between 3 hours and 6 hours post-injection. About 30% of the whole brain radioactivity was attributed to striatal uptake. By 48 hours post-injection, approximately 60% of the injected radioactivity has been excreted in the urine, with fecal excretion estimated to be approximately 14%.

13 NONCLINICAL TOXICOLOGY

13.1 Carcinogenesis, Mutagenesis, Impairment of Fertility

Studies on reproductive toxicity have not been conducted. Ioflupane showed no evidence of mutagenic potential in in vitro or in vivo mutagenicity studies. Studies to assess the carcinogenic potential of ioflupane have not been performed.

13.2 Animal Toxicology and/or Pharmacology

Single- and repeated-dose intravenous toxicity studies have been performed using ioflupane in rats, rabbits, and dogs. Additionally, single-dose acute toxicity studies have been performed in cynomolgus monkeys. No mortality or other toxicity was observed at doses up to 5,500 times the maximum clinical dose of DATSCAN; at doses greater than 1,500 times the maximum clinical dose, pharmacological responses such as mydriasis and hyperactivity were seen in some species.

14 CLINICAL STUDIES

14.1 Suspected Parkinsonian Syndromes

The safety and efficacy of DATSCAN were evaluated in two multicenter, single-arm, open-label studies (Study 1 and Study 2) that enrolled 284 adult patients with suspected PS.

In these studies, DATSCAN image interpretation was compared to a reference clinical diagnostic standard of "PS" or "non-PS". PS consisted of Parkinson's disease (PD), multiple system atrophy (MSA), and progressive supranuclear palsy (PSP). These conditions have been associated with dopaminergic neurodegeneration and DATSCAN imaging was not designed to distinguish among the conditions. Among the non-PS population, subjects with a history of the following conditions were included: vascular parkinsonism, psychogenic parkinsonism, essential tremor (ET), various forms of tremor, and other non-PS diagnoses; DATSCAN imaging was not designed to distinguish among these conditions.

Patients underwent SPECT imaging with a variety of multi-headed cameras or multi-detector single-slice systems 3 to 6 hours after DATSCAN administration. The DATSCAN activity in these two clinical studies ranged from 111 MBq to 201 MBq (3 mCi to 5.4 mCi) [median 167.8 MBq (4.5 mCi)]. Readers blinded to clinical information interpreted DATSCAN imaging as normal or abnormal [see Dosage and Administration (2.7)]. A normal image is inconsistent with clinical conditions associated with PS and an abnormal image is consistent with clinical conditions associated with PS.

Study 1 consisted of 99 patients with early features of Parkinsonism; patients with features suggestive of MSA or PSP were excluded. The baseline clinical diagnoses consisted of: probable PD (44%), possible PD (31%), "benign" PD (6%), possible ET (11%), and other diagnoses (7%). The patients were 44% female, 42% of age 65 years or over, and all were White. Study 1 readers had no other role in patient assessment. The reference clinical diagnostic standard consisted of the clinical diagnoses established by a consensus panel of movement disorder specialists that evaluated data inclusive through 36 months of follow-up.

Study 2 consisted of 185 patients with clinically established diagnosis of PS (PD, MSA, PSP) or ET. The baseline clinical diagnoses consisted of: PD (70%), MSA (10%), PSP (5%), and ET (15%). The patients were 35% female, 48% of age 65 years or over, and 99% were White. Study 2 readers included site investigators. The reference clinical diagnostic standard consisted of the investigator-determined baseline clinical diagnosis.

Table 4 shows the positive percent agreement and negative percent agreement of the DATSCAN image results with the reference clinical diagnostic standard. Positive percent agreement represents the percent of patients with abnormal DATSCAN images among all the patients with a clinical diagnostic reference standard of PS. Negative percent agreement represents the percent of patients with normal DATSCAN images among the patients with a non-PS clinical diagnostic reference standard.

Table 4: Positive and Negative Percent Agreements for Studies 1 and 2
 | Positive percent agreement (95 % CI) | Negative percent agreement (95 % CI)
Study 1 (patients with early signs and/or symptoms of PS)
Reader A, n = 99 | 77 (66, 87) | 96 (82, 100)
Reader B, n = 96 | 78 (66, 87) | 96 (82, 100)
Reader C, n = 98 | 79 (67, 87) | 96 (82, 100)
Study 2 (patients with established diagnoses of PS or ET)
Reader A, n = 185 | 93 (88, 97) | 96 (81, 100)
Reader B, n = 185 | 97 (93, 99) | 74 (54, 89)
Reader C, n = 185 | 96 (92, 99) | 85 (66, 96)
Reader D, n = 185 | 92 (87, 96) | 93 (76, 99)
Reader E, n = 185 | 94 (90, 97) | 93 (76, 99)

14.2 Suspected Dementia with Lewy Bodies

The evidence for the efficacy of DATSCAN in visualizing striatal dopamine transporters in adult patients with DLB is derived from the scientific literature. In 55 patients clinically diagnosed with DLB or with Alzheimer's disease, the results of consensus blinded visual assessment of the DATSCAN images were compared to neuropathological diagnosis made using standard international criteria at autopsy. The patients were 38% female and of ages 63 to 95 years (mean 77 years) at the time of DATSCAN imaging. The median administered DATSCAN activity was 150 MBq to 185 MBq (4.1 mCi to 4.9 mCi). DATSCAN images were rated as normal or abnormal [see Dosage and Administration (2.7)]. Based on autopsy diagnosis, the sensitivity and specificity of DATSCAN for DLB was 80% (95% CI 61% to 92%) and 92% (95% CI 74% to 99%), respectively.

The effectiveness of DATSCAN as a screening or confirmatory test and for monitoring disease progression or response to therapy has not been established.

16 HOW SUPPLIED/STORAGE AND HANDLING

How Supplied

DATSCAN (ioflupane I 123 injection) is a clear, colorless solution supplied in single-dose glass vials containing 185 MBq (5 mCi) in 2.5 mL at a concentration of 74 MBq/mL (2 mCi/mL) of ioflupane I 123 at calibration date and time. Each vial is enclosed in a lead container of appropriate thickness.

NDC 17156-210-01

Storage and Handling

Store DATSCAN at 20° to 25°C (68° to 77°F). This product does not contain a preservative. Store DATSCAN within the original lead container or equivalent radiation shielding.

Do not use DATSCAN preparations after the expiration date and time stated on the label.

This preparation is approved for use by persons licensed by the Illinois Emergency Management Agency pursuant to 32 IL. Adm. Code Section 330.260(a) and 335.4010 or equivalent licenses of the Nuclear Regulatory Commission or the relevant regulatory authority of an Agreement State.

17 PATIENT COUNSELING INFORMATION

Hypersensitivity Reactions

Inform the patient that hypersensitivity reactions, including dyspnea, edema, rash, erythema and pruritus, have been reported following DATSCAN administration [see Warnings and Precautions (5.1)].

Adequate Hydration

Instruct patients to drink a sufficient amount of water prior to and after receiving DATSCAN and to void frequently for the first 48 hours following DATSCAN administration [see Dosage and Administration (2.1)].

Lactation

Advise a lactating woman to interrupt breastfeeding and pump and discard breastmilk for at least 6 days (>10 physical half-lives) after DATSCAN administration in order to minimize radiation exposure to a breastfed infant [see Use in Specific Populations (8.2)].

Pregnancy

Advise a pregnant woman of the potential risks of fetal exposure to radiation doses with DATSCAN [see Use in Specific Populations (8.1)].

Manufactured and Distributed by
GE Healthcare, Medi-Physics, Inc.
Arlington Heights, IL 60004 U.S.A.

GE Healthcare

DATSCAN is a trademark of GE Healthcare or one of its subsidiaries.

GE and the GE Monogram are trademarks of General Electric Company.

© 2022 General Electric Company – All rights reserved.

43-2010F

PRINCIPAL DISPLAY PANEL - 2.5 mL Vial Label

GE Healthcare
NDC 17156-210-01

DaTscan™
Ioflupane I 123 Injection

Ioflupane I 123 185 MBq (5 mCi) in 2.5 mL
at calibration

Radiopharmaceutical for Intravenous Injection

Single-Dose Vial. Discard unused portion.

Rx ONLY

VOLUME: 2.5 mL

RADIOACTIVE
CONCENTRATION:
74 MBq/mL
(2 mCi/mL)

CALIB.
DATE:
DDMMMYY

CALIB.
TIME:
1200 XXX